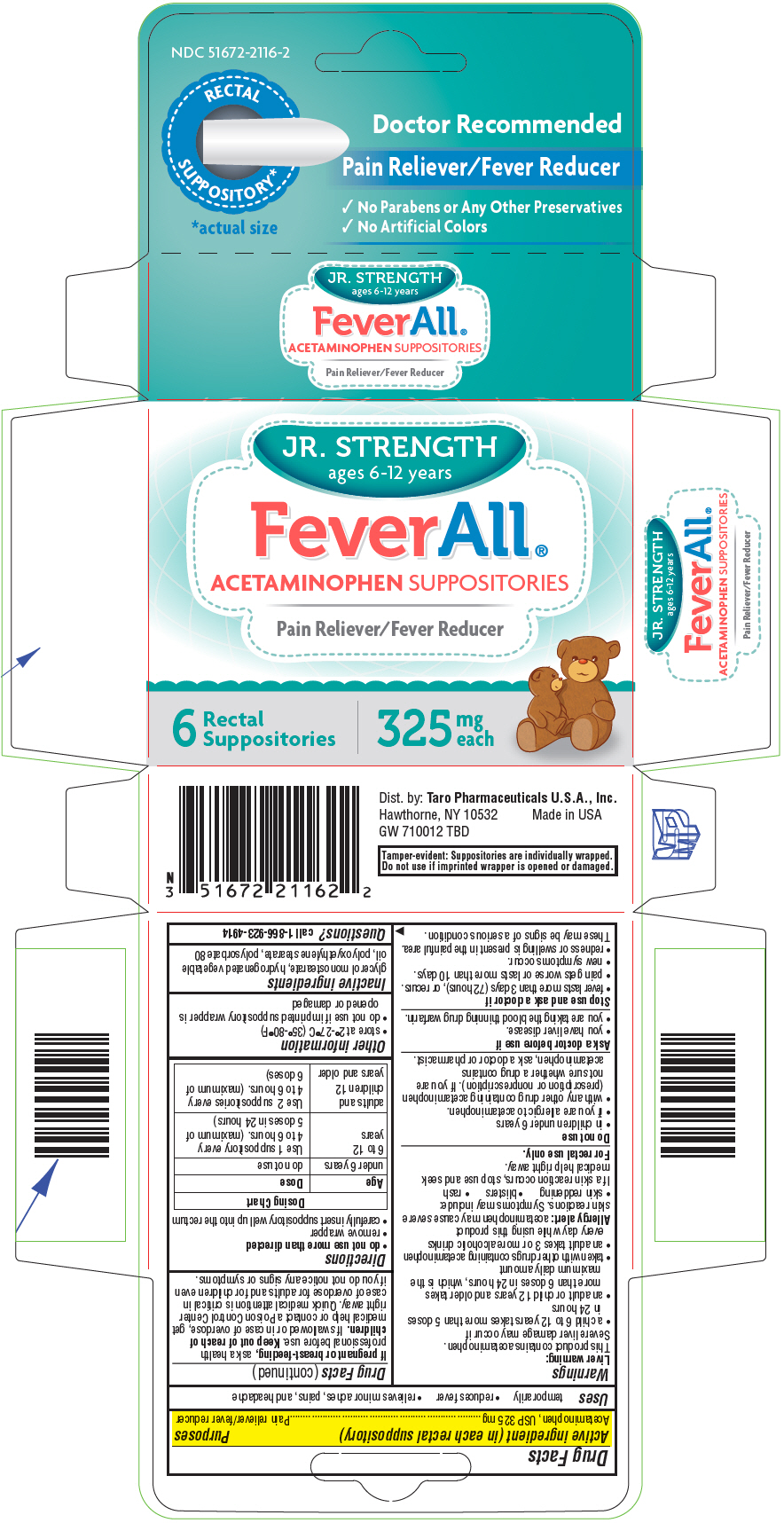 DRUG LABEL: Feverall 


NDC: 51672-2116 | Form: SUPPOSITORY
Manufacturer: Sun Pharmaceutical Industries, Inc.
Category: otc | Type: HUMAN OTC DRUG LABEL
Date: 20260202

ACTIVE INGREDIENTS: ACETAMINOPHEN 325 mg/1 1
INACTIVE INGREDIENTS: GLYCERYL MONOSTEARATE; HYDROGENATED PALM KERNEL OIL; PEG-100 STEARATE; POLYSORBATE 80

FeverAll®
Jr. Strength

Drug Facts

Active ingredient (in each rectal suppository)

Acetaminophen, USP 325 mg

Purposes

Pain reliever/fever reducer

Uses

temporarily

- reduces fever
- relieves minor aches, pains, and headache

Warnings

Liver warning

This product contains acetaminophen.

Severe liver damage may occur if

- a child 6 to 12 years takes more than 5 doses in 24 hours
- an adult or child 12 years and older takes more than 6 doses in 24 hours, which is the maximum daily amount
- taken with other drugs containing acetaminophen
- an adult takes 3 or more alcoholic drinks every day while using this product

Allergy alert:acetaminophen may cause severe skin reactions. Symptoms may include:

- skin reddening
- blisters
- rash

If a skin reaction occurs, stop use and seek medical help right away.

For rectal use only.

Do not use

- in children under 6 years
- if you are allergic to acetaminophen.
- with any other drug containing acetaminophen (prescription or nonprescription). If you are not sure whether a drug contains acetaminophen, ask a doctor or pharmacist.

Ask a doctor before use if

- you have liver disease.
- you are taking the blood thinning drug warfarin.

Stop use and ask a doctor if

- fever lasts more than 3 days (72 hours), or recurs.
- pain gets worse or lasts more than 10 days.
- new symptoms occur.
- redness or swelling is present in the painful area.

These may be signs of a serious condition.

KEEP OUT OF REACH OF CHILDREN

If pregnant or breast-feeding,ask a health professional before use. Keep out of reach of children.If swallowed or in case of overdose, get medical help or contact a Poison Control Center right away. Quick medical attention is critical in case of overdose for adults and for children even if you do not notice any signs or symptoms.

Directions

- do not use more than directed
- remove wrapper
- carefully insert suppository well up into the rectum

Dosing Chart
Age | Dose
under 6 years | do not use
6 to 12 years | Use 1 suppository every 4 to 6 hours. (maximum of 5 doses in 24 hours)
adults and children 12 years and older | Use 2 suppositories every 4 to 6 hours. (maximum of 6 doses)

Other information

- store at 2°-27°C (35°-80°F)
- do not use if imprinted suppository wrapper is opened or damaged

Inactive ingredients

glycerol monostearate, hydrogenated vegetable oil, polyoxyethylene stearate, polysorbate 80

Questions?

call 1-866-923-4914

Dist. by: Taro Pharmaceuticals U.S.A., Inc.
Hawthorne, NY 10532

PRINCIPAL DISPLAY PANEL - 325 mg Suppository Blister Pack Carton

NDC 51672-2116-2

RECTAL
SUPPOSITORY*

*actual size

Doctor Recommended

Pain Reliever/Fever Reducer

- No Parabens or Any Other Preservatives
- No Artificial Colors

JR. STRENGTH
ages 6-12 years

FeverAll®
ACETAMINOPHEN SUPPOSITORIES

Pain Reliever/Fever Reducer

6
Rectal
Suppositories

325
mg
each